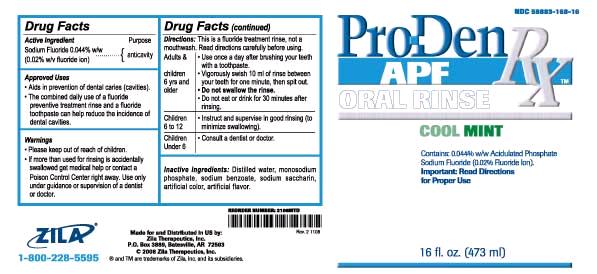 DRUG LABEL: Pro-Den Rx
NDC: 59883-168 | Form: GEL
Manufacturer: Zila Therapeutics, Inc.
Category: otc | Type: HUMAN OTC DRUG LABEL
Date: 20100816

ACTIVE INGREDIENTS: SODIUM FLUORIDE 0.044 mL/1 mL
INACTIVE INGREDIENTS: SODIUM BENZOATE; SACCHARIN SODIUM; WATER; SODIUM PHOSPHATE, MONOBASIC ANHYDROUS

Pro-Den Rx

Drug Facts

OTC - ACTIVE INGREDIENT

Sodium Fluoride 0.044% w/w (0.02% w/v fluoride ion)

OTC - PURPOSE

Anticavity

Approved Uses

- Aids in prevention of dental caries (cavities).
- The combined daily use of a fluoride preventive treatment rinse and a fluoride toothpaste can help reduce the incidence of dental cavities.

Warnings

- Please keep out of reach of children.
- If more than used for rinsing is accidentally swallowed get medical help or contact a Poison Control Center right away. Use only under guidance or supervision of a dentist or doctor.

Directions: This is a fluoride treatment rinse, not a mouthwash. Read directions carefully before using.

Adults and Children 6 yrs and older | Use once a day after brushing your teeth with a toothpaste. Vigorously swish 10 ml of rinse between your teeth for one minute, then spit out. Do not swallow the rinse. Do not eat or drink for 30 minutes after rinsing.
Children 6 to 12 | Instruct and supervise in good rinsing (to minimize swallowing).
Children Under 6 | Consult a dentist or doctor.

Inactive Ingredients:

Distilled water, monosodium phosphate, sodium benzoate, sodium saccharin, artificial color, artificial flavor.

Made for and Distributed in US by:
Zila Therapeutics, Inc.,

P.O. Box 3889, Batesville, AR 72503

1-800-228-5595